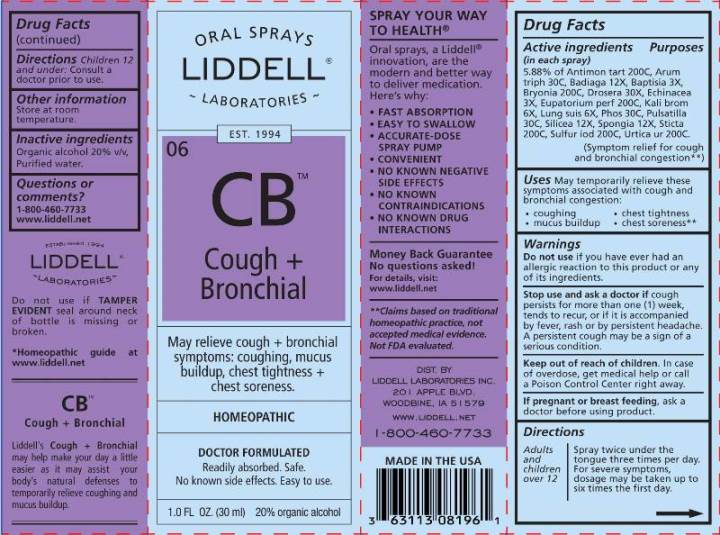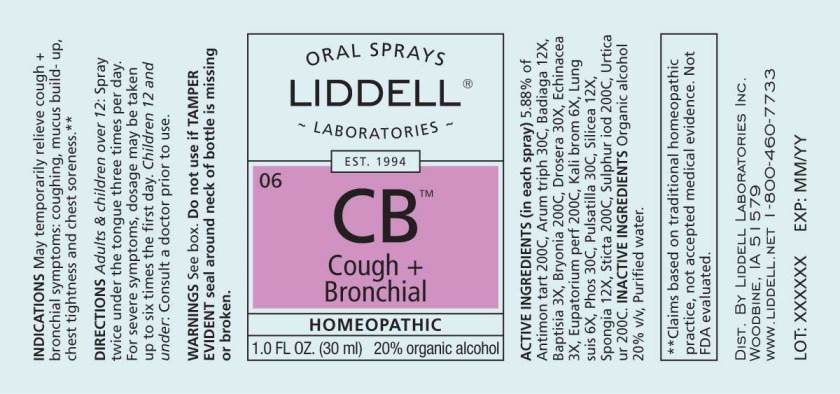 DRUG LABEL: Cough plus Bronchial
NDC: 50845-0246 | Form: SPRAY
Manufacturer: Liddell Laboratories, Inc.
Category: homeopathic | Type: HUMAN OTC DRUG LABEL
Date: 20240701

ACTIVE INGREDIENTS: ANTIMONY POTASSIUM TARTRATE 200 [hp_C]/1 mL; ARISAEMA TRIPHYLLUM ROOT 30 [hp_C]/1 mL; SPONGILLA LACUSTRIS 12 [hp_X]/1 mL; BAPTISIA TINCTORIA ROOT 3 [hp_X]/1 mL; BRYONIA ALBA ROOT 200 [hp_C]/1 mL; DROSERA ROTUNDIFOLIA WHOLE 3 [hp_X]/1 mL; ECHINACEA ANGUSTIFOLIA WHOLE 3 [hp_X]/1 mL; EUPATORIUM PERFOLIATUM FLOWERING TOP 200 [hp_C]/1 mL; POTASSIUM BROMIDE 6 [hp_X]/1 mL; SUS SCROFA LUNG 6 [hp_X]/1 mL; PHOSPHORUS 30 [hp_C]/1 mL; PULSATILLA PRATENSIS WHOLE 30 [hp_C]/1 mL; SILICON DIOXIDE 12 [hp_X]/1 mL; SPONGIA OFFICINALIS SKELETON, ROASTED 12 [hp_X]/1 mL; LOBARIA PULMONARIA 200 [hp_C]/1 mL; SULFUR IODIDE 200 [hp_C]/1 mL; URTICA URENS WHOLE 200 [hp_C]/1 mL
INACTIVE INGREDIENTS: WATER; ALCOHOL

DRUG FACTS:

ACTIVE INGREDIENTS:

(in each spray): 5.88% of Antimonium Tartaricum 200C, Arum Triphyllum 30C, Badiaga 12X, Baptisia Tinctoria 3X, Bryonia (Alba) 200C, Drosera (Rotundifolia) 30X, Echinacea (Angustifolia) 3X, Eupatorium Perfoliatum 200C, Kali Bromatum 6X, Lung Suis 6X, Phosphorus 30C, Pulsatilla (Pratensis) 30C, Silicea 12X, Spongia Tosta 12X, Sticta Pulmonaria 200C, Sulphur Iodatum 200C, Urtica Urens 200C.

USES:

May temporarily relieve these symptoms associated with cough and bronchial congestion:

• coughing

• mucous buildup

• chest tightness

• chest soreness**

**Claims based on traditional homeopathic practice, not accepted medical evidence. Not FDA evaluated.

WARNINGS:

Do not use if you have ever had an allergic reaction to this product or any of its ingredients.

Stop use and ask a doctor if cough persists for more than one (1) week, tends to recur, or if it is accompanied by fever, rash or by persistent headache. A persistent cough may be a sign of a serious condition.

Keep out of reach of children. In case of overdose, get medical help or call a Poison Control Center right away.

If pregnant or breast feeding, ask a doctor before using product.

Do not use if TAMPER EVIDENT seal around neck of bottle is missing or broken.

Other information

Store at room temperature.

Keep out of reach of children. In case of overdose, get medical help or call a Poison Control Center right away.

DIRECTIONS:

Adults and children over 12 Spray twice under the tongue three times per day. For severe symptoms, dosage may be taken up to six times the first day.

Children 12 and under Consult a doctor prior to use.

INDICATIONS:

May temporarily relieve these symptoms associated with cough and bronchial congestion:

• coughing

• mucous buildup

• chest tightness

• chest soreness**

**Claims based on traditional homeopathic practice, not accepted medical evidence. Not FDA evaluated.

INACTIVE INGREDIENTS:

Organic alcohol 20% v/v, Purified water

QUESTIONS:

DIST. BY LIDDELL LABORATORIES INC.
WOODBINE, IA 51579
WWW.LIDDELL.NET

1-800-460-7733

PACKAGE LABEL DISPLAY:

ORAL SPRAYS

LIDDELL

LABORATORIES

EST. 1994

06 CB

Cough +

Bronchial

May relieve cough + bronchial

symptoms: coughing, mucous

buildup, chest tightness +

chest soreness.

HOMEOPATHIC

DOCTOR FORMULATED
Readily absorbed. Safe.
No known side effects. Easy to use.

1.0 FL OZ. (30 ml)